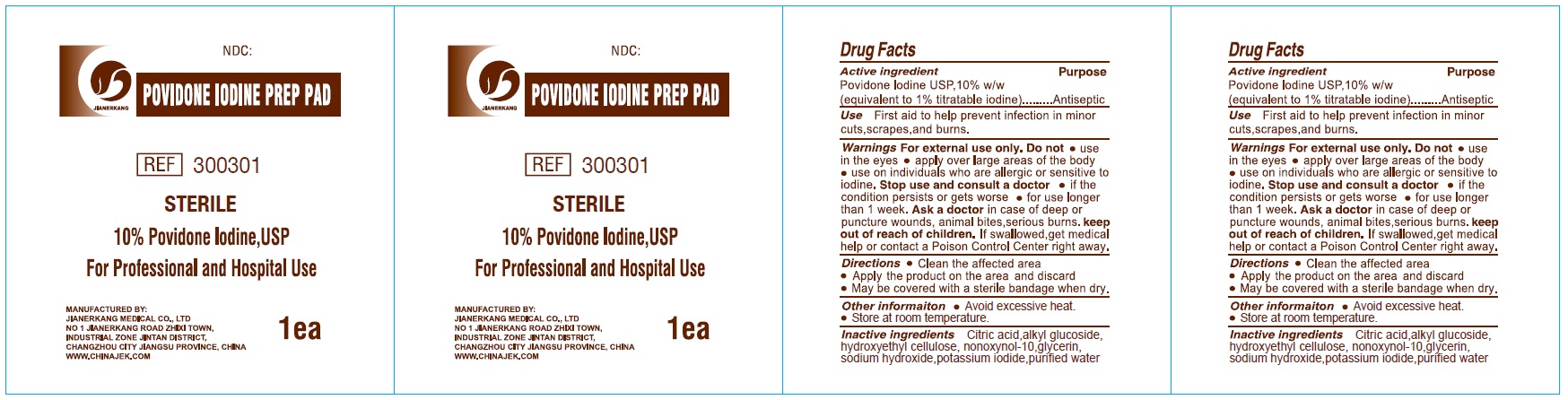 DRUG LABEL: POVIDONE IODINE PREP PAD Sterile
NDC: 34645-0022 | Form: CLOTH
Manufacturer: Jianerkang Medical Co., Ltd
Category: otc | Type: HUMAN OTC DRUG LABEL
Date: 20231023

ACTIVE INGREDIENTS: POVIDONE-IODINE 100 mg/1 mL
INACTIVE INGREDIENTS: CITRIC ACID MONOHYDRATE; HYDROXYETHYL CELLULOSE, UNSPECIFIED; NONOXYNOL-10; GLYCERIN; SODIUM HYDROXIDE; POTASSIUM IODIDE; WATER

POVIDONE IODINE PREP PAD Sterile

Active ingredient

Povidone Iodine USP, 10% w/w (equivalent to 1% titratable iodine)

Purpose

Antiseptic

Use

First aid to help prevent infection in minor cuts, scrapes, and burns.

Warnings

For external use only.

Do not

- use in the eyes
- apply over large over large areas of the body
- use on individuals who are allergic or sensitive to iodine.

Stop use and consult a doctor

- if the condition persists or gets worse
- for use longer than 1 week.

Ask a doctor

in case of deep or puncture wounds, animal bites, serious burns.

keep out of reach of children.

If swallowed, get medical help or contact a Poison Control Center right away.

Directions

- Clean the affected area
- Apply the product on the area and discard
- May be covered with a sterile bandage when dry.

Other information

- Avoid excessive heat.
- Store at room temperature.

Inactive ingredients

Citric acid, alkyl glucoside, hydroxyethyl cellulose, nonoxynol-10, glycerin, sodium hydroxide, potassium iodide, purified water